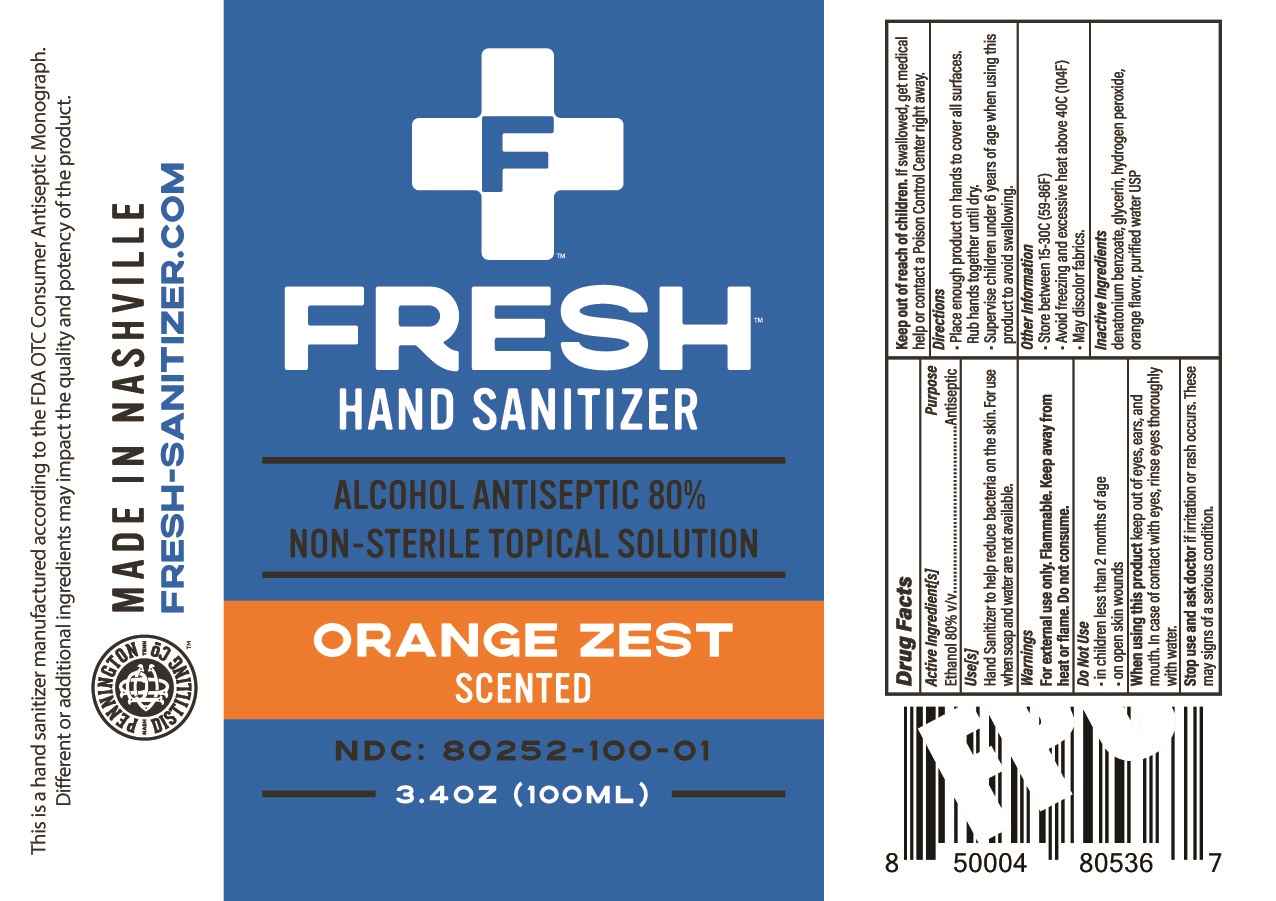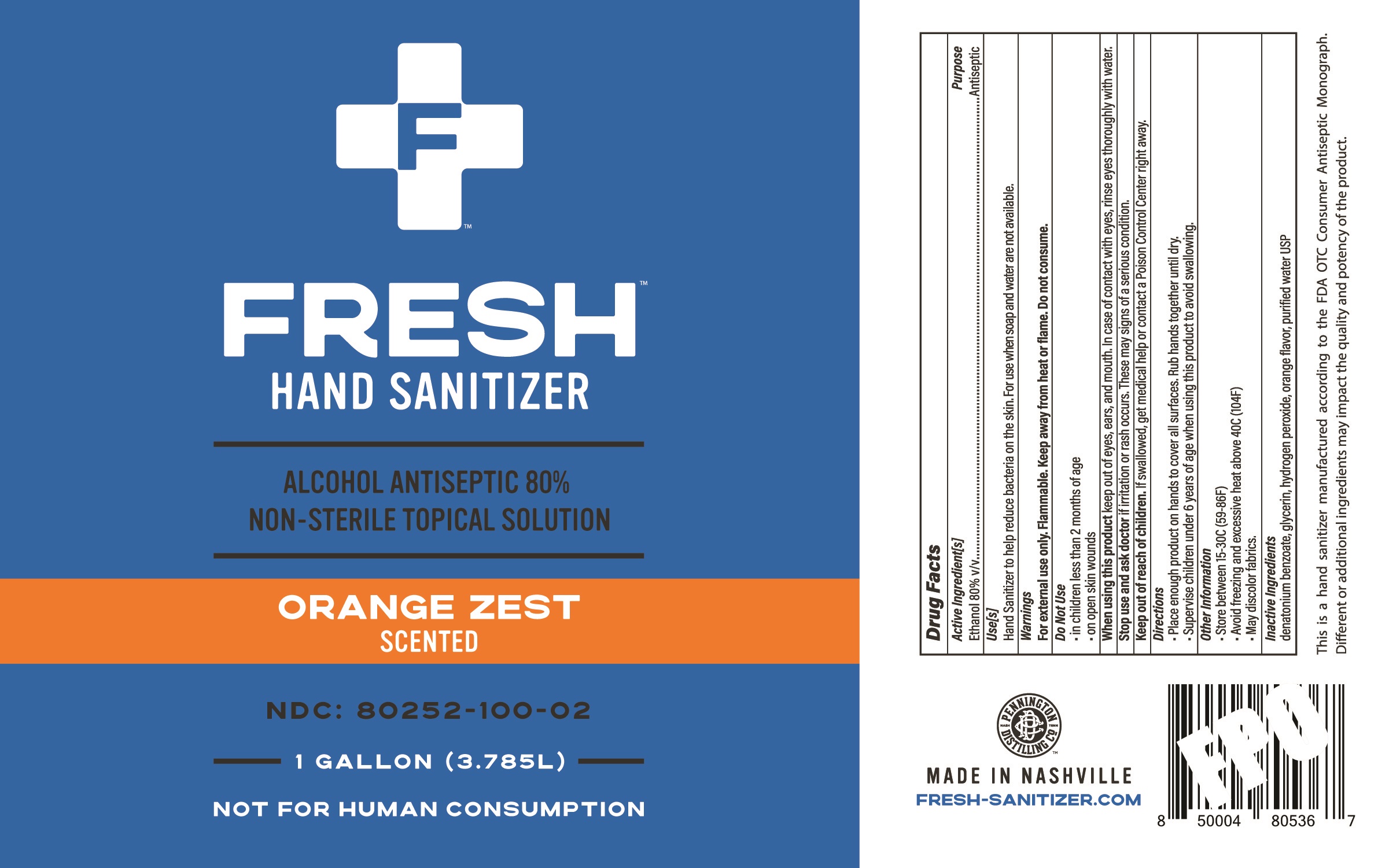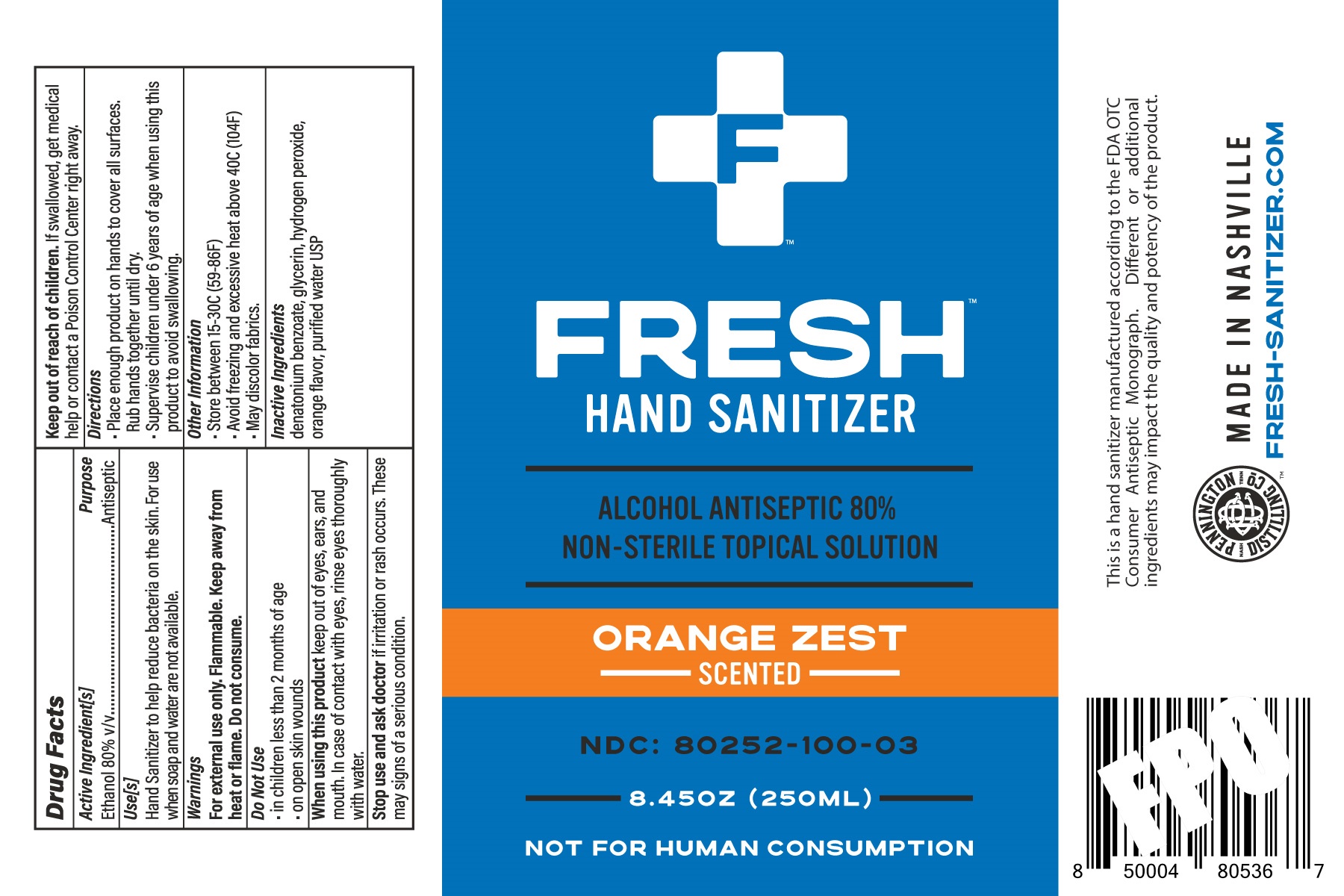 DRUG LABEL: Hand Sanitizer
NDC: 80252-100 | Form: SOLUTION
Manufacturer: Fresh Sanitizer, LLC
Category: otc | Type: HUMAN OTC DRUG LABEL
Date: 20201001

ACTIVE INGREDIENTS: ALCOHOL 80 mL/100 mL
INACTIVE INGREDIENTS: DENATONIUM BENZOATE 0.000411 g/100 mL; GLYCERIN 1.421 mL/100 mL; HYDROGEN PEROXIDE 0.1251 mL/100 mL; WATER 18.4539 mL/100 mL

Active Ingredient(s)

Alcohol 80% v/v. Purpose: Antiseptic

Purpose

Antiseptic, Hand Sanitizer

Use

Hand Sanitizer to help reduce bacteria on the skin. For use when soap and water are not available.

Warnings

For external use only. Flammable. Keep away from heat or flame. Do not consume.

Do not use

- in children less than 2 months of age
- on open skin wounds

When using this product keep out of eyes, ears, and mouth. In case of contact with eyes, rinse eyes thoroughly with water.
Stop use and ask a doctor if irritation or rash occurs. These may be signs of a serious condition.
Keep out of reach of children. If swallowed, get medical help or contact a Poison Control Center right away.

Stop use and ask a doctor if irritation or rash occurs. These may be signs of a serious condition.

Keep out of reach of children. If swallowed, get medical help or contact a Poison Control Center right away.

Directions

- Place enough product on hands to cover all surfaces. Rub hands together until dry.
- Supervise children under 6 years of age when using this product to avoid swallowing.

Other information

- Store between 15-30C (59-86F)
- Avoid freezing and excessive heat above 40C (104F)
- May discolor fabrics.

Inactive ingredients

denatonium benzoate, glycerin, hydrogen peroxide, orange flavor, purified water USP

Package Label - Principal Display Panel

100 mL

NDC: 80252-100-01

3785 mL or 3.785L or 1 Gallon

NDC: 80252-100-02

250mL

NDC: 80252-100-03